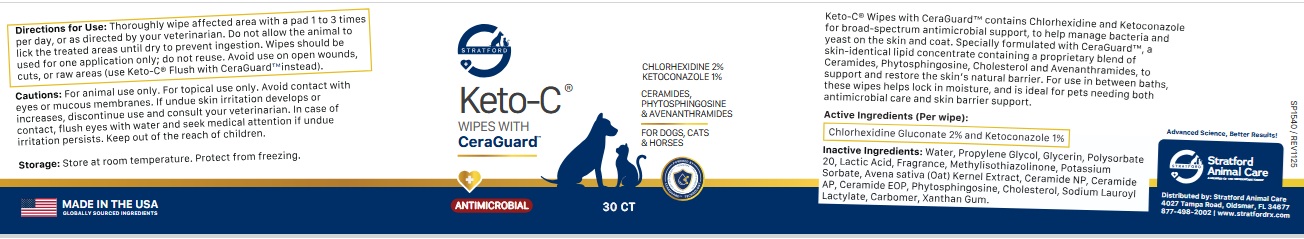 DRUG LABEL: STRATFORD Keto-C WIPES WITH CeraGuard
NDC: 86069-139 | Form: CLOTH
Manufacturer: Stratford Care Usa, Inc.
Category: animal | Type: OTC ANIMAL DRUG LABEL
Date: 20260204

ACTIVE INGREDIENTS: CHLORHEXIDINE GLUCONATE 2 g/100 mL; KETOCONAZOLE 1 g/100 mL
INACTIVE INGREDIENTS: WATER; PROPYLENE GLYCOL; GLYCERIN; POLYSORBATE 20; LACTIC ACID, UNSPECIFIED FORM; METHYLISOTHIAZOLINONE; POTASSIUM SORBATE; OAT; CERAMIDE NP; CERAMIDE AP; CERAMIDE 9; PHYTOSPHINGOSINE; CHOLESTEROL; SODIUM LAUROYL LACTYLATE; CARBOMER HOMOPOLYMER, UNSPECIFIED TYPE; XANTHAN GUM

STRATFORD Keto-C® WIPES WITH CeraGuardTM

Keto-C® Wipes with CeraGuardTM contains Chlorhexidine and Ketoconazole for broad-spectrum antimicrobial support, to help manage bacteria and yeast on the skin and coat. Specially formulated with CeraGuardTM, a skin-identical lipid concentrate containing a proprietary blend of Ceramides, Phytosphingosine, Cholesterol and Avenanthramides, to support and restore the skin's natural barrier. For use in between baths, these wipes helps lock in moisture, and is ideal for pets needing both antimicrobial care and skin barrier support.

Active Ingredients (Per wipe):

Chlorhexidine Gluconate 2% and Ketoconazole 1%

Inactive Ingredients:

Water, Propylene Glycol, Glycerin, Polysorbate 20, Lactic Acid, Fragrance, Methylisothiazolinone, Potassium Sorbate, Avena sativa (Oat) Kernel Extract, Ceramide NP, Ceramide AP, Ceramide EOP, Phytosphingosine, Cholesterol, Sodium Lauroyl Lactylate, Carbomer, Xanthan Gum.

Directions for Use:

Thoroughly wipe affected area with a pad 1 to 3 times per day, or as directed by your veterinarian. Do not allow the animal to lick the treated areas until dry to prevent ingestion. Wipes should be used for one application only; do not reuse. Avoid use on open wounds, cuts, or raw areas (use Keto-C® Flush with CeraGuardTM instead).

Cautions:

For animal use only. For topical use only. Avoid contact with eyes or mucous membranes. If undue skin irritation develops or increases, discontinue use and consult your veterinarian. In case of contact, flush eyes with water and seek medical attention if undue irritation persists. Keep out of the reach of children.

Storage:

Store at room temperature. Protect from freezing.

CERAMIDES, PHYTOSPHINGOSINE & AVENANTHRAMIDES

FOR DOGS, CATS & HORSES

ANTIMICROBIAL

Advanced Science, Better Results!

Stratford Animal Care
A MEMBER OF THE SWEDENCARE FAMILY

Distributed by: Stratford Animal Care
4027 Tampa Road, Oldsmar, FL 34677
877-498-2002 | www.stratfordrx.com

MADE IN THE USA
GLOBALLY SOURCED INGREDIENTS